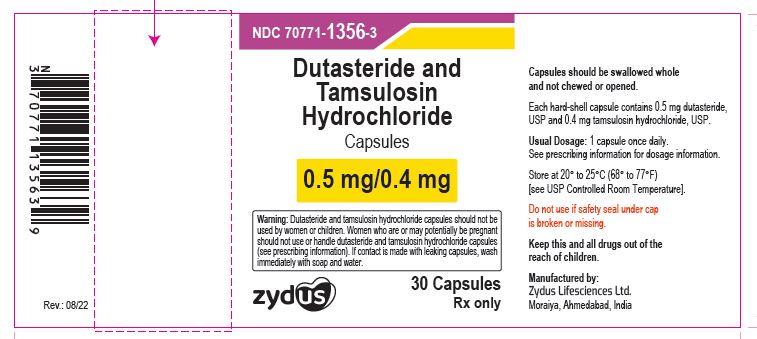 DRUG LABEL: Dutasteride and tamsulosin hydrochloride
NDC: 70771-1356 | Form: CAPSULE
Manufacturer: Zydus Lifesciences Limited
Category: prescription | Type: HUMAN PRESCRIPTION DRUG LABEL
Date: 20241128

ACTIVE INGREDIENTS: DUTASTERIDE 0.5 mg/1 1; TAMSULOSIN HYDROCHLORIDE 0.4 mg/1 1
INACTIVE INGREDIENTS: ALCOHOL; AMMONIA; BUTYL ALCOHOL; BUTYLATED HYDROXYTOLUENE; CARRAGEENAN; CELLULOSE, MICROCRYSTALLINE; FERRIC OXIDE YELLOW; FERROSOFERRIC OXIDE; GELATIN; GLYCERIN; GLYCERYL MONO- AND DICAPRYLOCAPRATE; HYPROMELLOSES; ISOPROPYL ALCOHOL; METHACRYLIC ACID AND ETHYL ACRYLATE COPOLYMER; METHYLPARABEN; POTASSIUM CHLORIDE; POTASSIUM HYDROXIDE; PROPYLENE GLYCOL; PROPYLPARABEN; SHELLAC; TALC; TITANIUM DIOXIDE; TRIACETIN

DUTASTERIDE AND TAMSULOSIN HYDROCHLORIDE CAPSULES

PACKAGE LABEL.PRINCIPAL DISPLAY PANEL

NDC 70771-1356-3

Dutasteride and tamsulosin hydrochloride Capsules, 0.4/0.5 mg

Rx only

30 Capsules